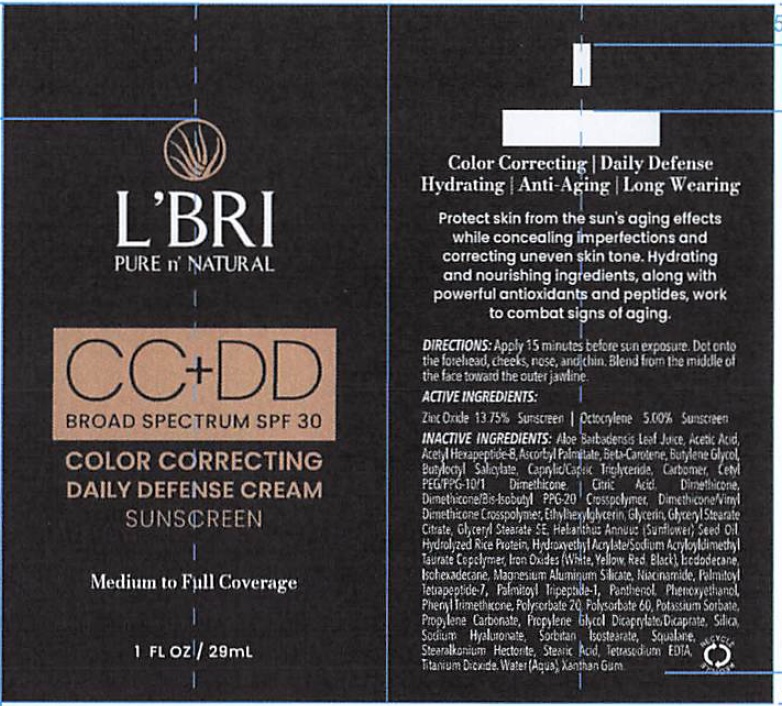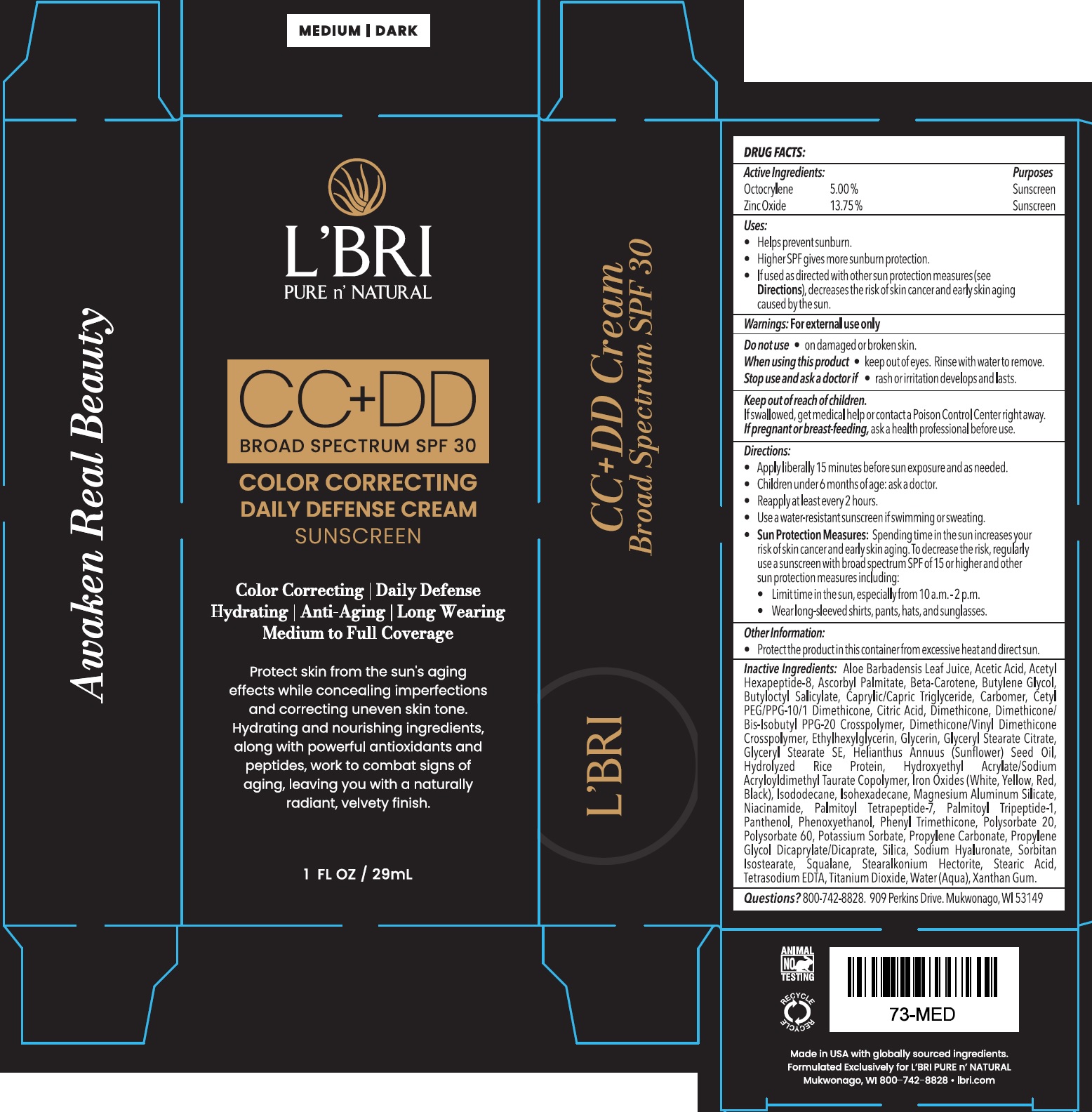 DRUG LABEL: L Bri CC DD Color Correcting Daily Defense Sunscreen SPF 30 Medium Dark
NDC: 71238-914 | Form: CREAM
Manufacturer: L'BRI Health & Beauty
Category: otc | Type: HUMAN OTC DRUG LABEL
Date: 20251209

ACTIVE INGREDIENTS: OCTOCRYLENE 50 mg/1 mL; ZINC OXIDE 137.5 mg/1 mL
INACTIVE INGREDIENTS: ALOE VERA LEAF JUICE; ACETIC ACID; ACETYL HEXAPEPTIDE-8 AMIDE; ASCORBYL PALMITATE; BETA-CAROTENE; BUTYLENE GLYCOL; BUTYLOCTYL SALICYLATE; CAPRYLIC/CAPRIC TRIGLYCERIDE; CARBOMER HOMOPOLYMER, UNSPECIFIED TYPE; CITRIC ACID MONOHYDRATE; DIMETHICONE; DIMETHICONE/BIS-ISOBUTYL PPG-20 CROSSPOLYMER; ETHYLHEXYLGLYCERIN; GLYCERIN; GLYCERYL STEARATE CITRATE; GLYCERYL STEARATE SE; SUNFLOWER OIL; FERRIC OXIDE RED; ISODODECANE; ISOHEXADECANE; MAGNESIUM ALUMINUM SILICATE; NIACINAMIDE; PALMITOYL TETRAPEPTIDE-7; PALMITOYL TRIPEPTIDE-1; PANTHENOL; PHENOXYETHANOL; PHENYL TRIMETHICONE; POLYSORBATE 20; POLYSORBATE 60; POTASSIUM SORBATE; PROPYLENE CARBONATE; PROPYLENE GLYCOL DICAPRYLATE/DICAPRATE; SILICA; SODIUM HYALURONATE; SORBITAN ISOSTEARATE; SQUALANE; STEARALKONIUM HECTORITE; STEARIC ACID; EDETATE SODIUM; TITANIUM DIOXIDE; WATER; XANTHAN GUM

L'Bri CC+DD Color Correcting Daily Defense Sunscreen SPF 30, Medium/Dark

Active Ingredients:

Octocrylene 5.00%
Zinc Oxide 13.75%

Purpose

Sunscreen

Uses:

- Helps prevent sunburn.
- Higher SPF gives more sunburn protection.
- If used as directed with other sun protection measures (see Directions), decreases the risk of skin cancer and early skin aging caused by the sun.

Warnings:

For external use only

Do not use

- on damaged or broken skin.

When using this product

- keep out of eyes. Rinse with water to remove.

Stop use and ask a doctor if

- rash or irritation develops and lasts.

Keep out of reach of children.

If swallowed, get medical help or contact a Poison Control Center right away.

If pregnant or breast-feeding,

ask a health professional before use.

Directions:

- Apply liberally 15 minutes before sun exposure and as needed.
- Children under 6 months of age: ask a doctor.
- Reapply at least every 2 hours.
- Use a water-resistant sunscreen if swimming or sweating.
- Sun Protection Measures: Spending time in the sun increases your risk of skin cancer and early skin aging. To decrease the risk, regularly use a sunscreen with a broad spectrum SPF of 15 or higher and other sun protection measures including:
- Limit time in sun, especially from 10 a.m.-2 p.m.
- Wear long-sleeved shirts, pants, hats and sunglasses.

Other Information:

- Protect the product in this container from excessive heat and direct sun.

Inactive Ingredients:

Aloe Barbadensis Leaf Juice, Acetic Acid, Acetyl Hexapeptide-8, Ascorbyl Palmitate, Beta-Carotene, Butylene Glycol, Butyloctyl Salicylate, Caprylic/Capric Triglyceride, Carbomer, Cetyl PEG/PPG-10/1 Dimethicone, Citric Acid, Dimethicone, Dimethicone/Bis-Isobutyl PPG-20 Crosspolymer, Dimethicone/Vinyl Dimethicone Crosspolymer, Ethylhexylglycerin, Glycerin, Glyceryl Stearate Citrate, Glyceryl Stearate SE, Helianthus Annuus (Sunflower) Seed Oil, Hydrolyzed Rice Protein, Hydroxyethyl Acrylate/Sodium Acryloyldimethyl Taurate Copolymer, Iron Oxides (White, Yellow, Red, Black), Isododecane, Isohexadecane, Magnesium Aluminum Silicate, Niacinamide, Palmitoyl Tetrapeptide-7, Palmitoyl Tripeptide-1, Panthenol, Phenoxyethanol, Phenyl Trimethicone, Polysorbate 20, Polysorbate 60, Potassium Sorbate, Propylene Carbonate, Propylene Glycol Dicaprylate/Dicaprate, Silica, Sodium Hyaluronate, Sorbitan Isostearate, Squalane, Stearalkonium Hectorite, Stearic Acid, Tetrasodium EDTA, Titanium Dioxide, Water (Aqua), Xanthan Gum.

Question?

800-742-8828. 909 Perkins Drive. Mukwonago, WI 53149